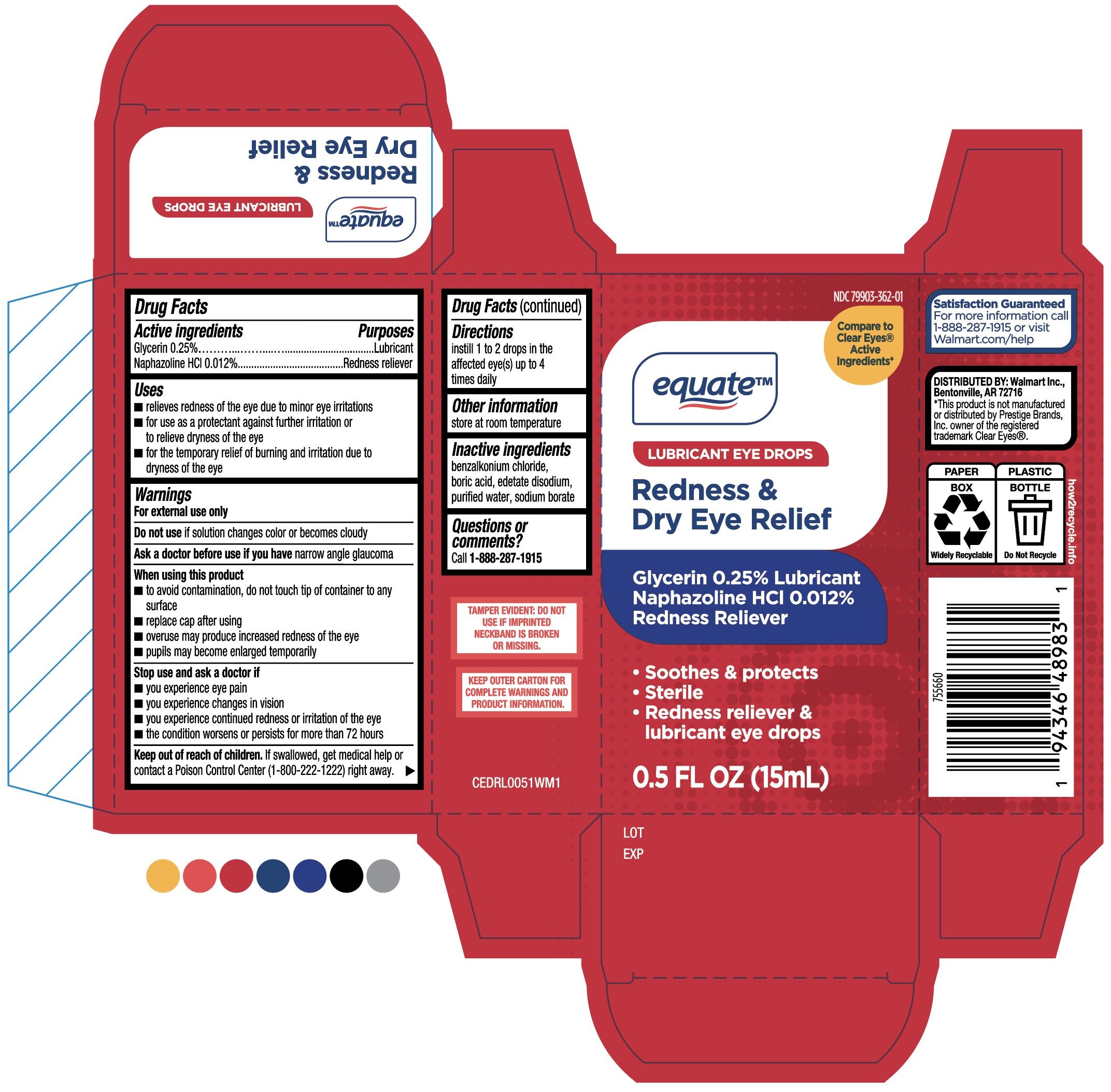 DRUG LABEL: Redness and Dry Eye Relief
NDC: 55651-620 | Form: SOLUTION
Manufacturer: KC Pharmaceuticals, Inc
Category: otc | Type: HUMAN OTC DRUG LABEL
Date: 20251221

ACTIVE INGREDIENTS: GLYCERIN 0.25 g/100 mL; NAPHAZOLINE HYDROCHLORIDE 0.012 g/100 mL
INACTIVE INGREDIENTS: EDETATE DISODIUM; BENZALKONIUM CHLORIDE; SODIUM BORATE; WATER; BORIC ACID

KC (MFG) for Walmart (PLD) NDC: 79903-362-01
Equate Redness & Dry Eye Relief

Active ingredients
Glycerin 0.25%
Naphazoline HCI 0.012%

PURPOSE

Active ingredients Purposes
Glycerin 0.25%........................................................Lubricant
Naphazoline HCI 0.012%........................................Redness reliever

Keep out of reach of children. If swallowed, get medical help or contact a Poison Control Center
(1-800-222-1222) right away.

Inactive Ingredients

benzalkonium chloride, boric acid, edetate disodium,
purified water, sodium borate

Directions:
instill 1 to 2 drops Ianthe affected eye(s) up to 4 times daily

Uses
■ relieves redness of the eye due to minor eye irritations
■ for use as a protectant against further irritation or to relieve dryness of the eye
■ for the temporary relief of burning and irritation due to dryness of the eye

Warnings
For external use only
Do not use if solution changes color or becomes cloudy
Ask a doctor before use if you have narrow angle glaucoma
When using this product
■ to avoid contamination, do not touch tip of container to any surface
■ replace cap after using
■ overuse may produce increased redness of the eye
■ pupils may become enlarged temporarily
Stop use and ask a doctor if
■ you experience eye pain
■ you experience changes in vision
■ you experience continued redness or irritation of the eye
■ the condition worsens or persists for more than 72 hours